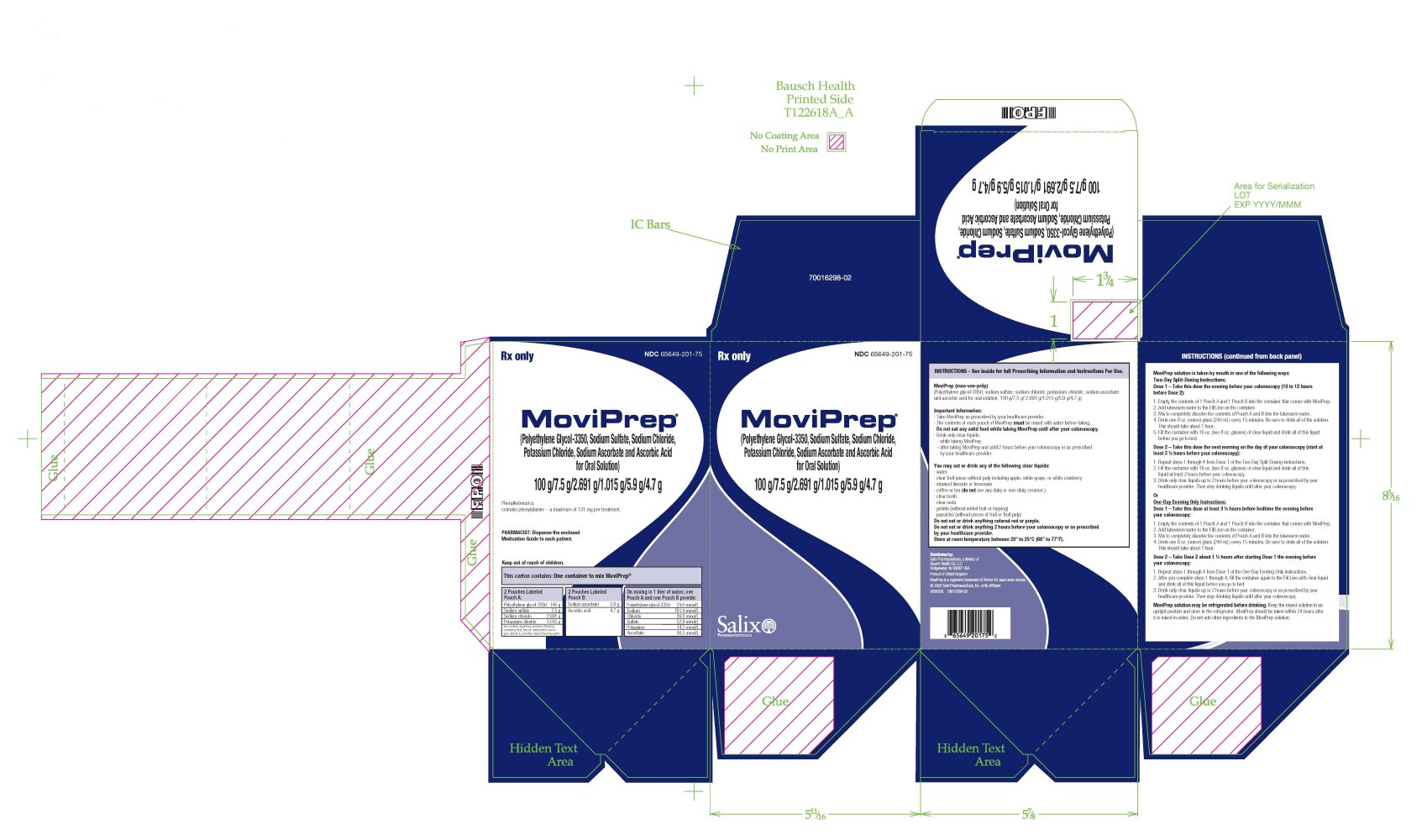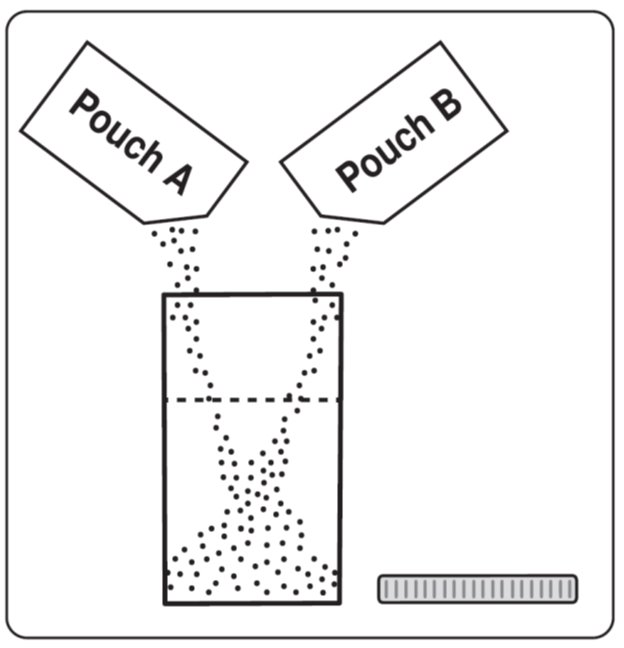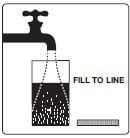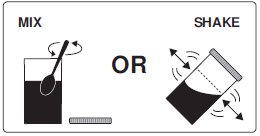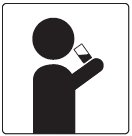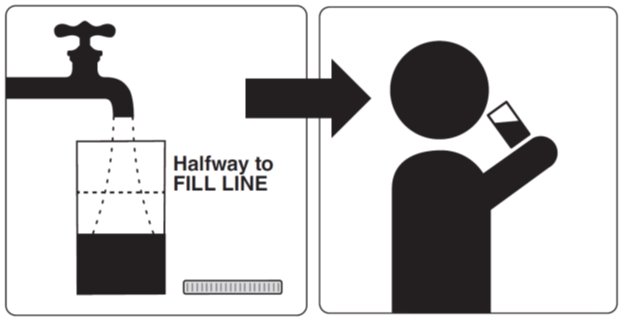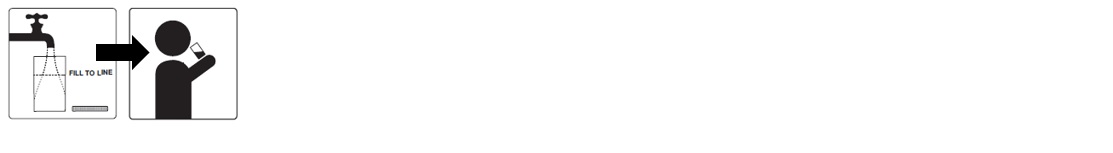 DRUG LABEL: MoviPrep
NDC: 65649-201 | Form: KIT | Route: ORAL
Manufacturer: Salix Pharmaceuticals, Inc.
Category: prescription | Type: HUMAN PRESCRIPTION DRUG LABEL
Date: 20251031

ACTIVE INGREDIENTS: POLYETHYLENE GLYCOL 3350 100 g/1 L; SODIUM SULFATE 7.5 g/1 L; SODIUM CHLORIDE 2.69 g/1 L; POTASSIUM CHLORIDE 1.015 g/1 L; ASCORBIC ACID 4.7 g/1 L; SODIUM ASCORBATE 5.9 g/1 L
INACTIVE INGREDIENTS: ASPARTAME; LEMON; ACESULFAME POTASSIUM

HIGHLIGHTS OF PRESCRIBING INFORMATION

These highlights do not include all the information needed to use MOVIPREP safely and effectively. See full prescribing information for MOVIPREP.
MOVIPREP® (polyethylene glycol 3350, sodium sulfate, sodium chloride, potassium chloride, sodium ascorbate, and ascorbic acid for oral solution)
Initial U.S. Approval: 2006

1 INDICATIONS AND USAGE

MoviPrep is an osmotic laxative indicated for cleansing of the colon as a preparation for colonoscopy in adults. (1)

2 DOSAGE AND ADMINISTRATION

Preparation and Administration:

- Two doses of MoviPrep are required for a complete preparation for colonoscopy, using a “Two-Day” preferred method or “One-Day” alternative method dosing regimen. (2.1)
- MoviPrep must be reconstituted in water prior to ingestion. (2.1)
- Additional clear liquids must be consumed after each dose of MoviPrep in both dosing regimens. (2.1, 5.1)
- Do not take other laxatives while taking MoviPrep. (2.1, 5.5)
- Do not take oral medications within 1 hour of starting each dose. (2.1)

Dosing Regimen:

- Two-Day (Split-Dose) (Preferred Method): Dose 1 the evening before the colonoscopy, and Dose 2 the morning of the colonoscopy (approximately 12 hours after the start of Dose 1, and at least 3 ½ hours prior to the colonoscopy). (2.2)
- One-Day (Evening Only) (Alternative Method): Dose 1 at least 3 ½ hours prior to bedtime the evening before the colonoscopy and Dose 2 approximately 1 ½ hours after starting Dose 1 the evening before the colonoscopy. (2.3)
- For complete information on dosing, preparation and administration see full prescribing information (2.1, 2.2, 2.3)

3 DOSAGE FORMS AND STRENGTHS

For Oral Solution: 2 pouches labeled Pouch A and 2 pouches labeled Pouch B. (3)

- Each Pouch A contains 100 grams of polyethylene glycol (PEG) 3350, 7.5 grams of sodium sulfate, 2.691 grams of sodium chloride, and 1.015 grams of potassium chloride. Pouch A contains lemon flavoring. (3)
- Each Pouch B contains 4.7 grams of ascorbic acid and 5.9 grams of sodium ascorbate. (3)

4 CONTRAINDICATIONS

- Gastrointestinal (GI) obstruction (4, 5.6)
- Bowel perforation (4, 5.6)
- Gastric retention (4)
- Ileus (4)
- Toxic colitis or toxic megacolon (4)
- Hypersensitivity to any ingredient in MoviPrep (4, 5.10)

5 WARNINGS AND PRECAUTIONS

- Risk of fluid and electrolyte abnormalities: Encourage adequate hydration, assess concurrent medications, and consider laboratory assessments prior to and after use. (5.1, 7.1)
- Cardiac arrhythmias: Consider pre-dose and post-colonoscopy ECGs in patients at increased risk. (5.2)
- Seizures: Use caution in patients with a history of seizures and patients at increased risk of seizure, including medications that lower the seizure threshold. (5.3, 7.1)
- Patients with renal impairment or taking concomitant medications that affect renal function: Use caution, ensure adequate hydration and consider laboratory testing. (5.4, 7.1, 8.6)
- Colonic mucosal ulcerations: Consider potential for ulcerations when interpreting colonoscopy findings in patients with known or suspected inflammatory bowel disease. (5.5)
- Suspected GI obstruction or perforation: Rule out the diagnosis before administration. (5.6)
- Patients at risk for aspiration: Observe during administration. (5.7)
- Glucose-6-phosphate dehydrogenase deficiency (G-6-PD): Use with caution. (5.8)
- Risks in patients with phenylketonuria: Contains phenylalanine (5.9)
- Hypersensitivity reactions, including anaphylaxis: Inform patients to seek immediate medical care if symptoms occur. (5.10)

6 ADVERSE REACTIONS

Most common adverse reactions (≥ 5%) are:

- Two-Day (Split-Dose): malaise, nausea, abdominal pain, vomiting, and upper abdominal pain. (6.1)
- One-Day (Evening-Only): abdominal distension, anal discomfort, thirst, nausea, abdominal pain, sleep disorder, rigors, hunger, malaise, vomiting, and dizziness. (6.1)

To report SUSPECTED ADVERSE REACTIONS, contact Salix Pharmaceuticals at 1-800-321-4576 or FDA at 1-800-FDA-1088 or www.fda.gov/medwatch.

7 DRUG INTERACTIONS

Drugs that increase risk for fluid and electrolyte imbalance. (7.1)

FULL PRESCRIBING INFORMATION

1 INDICATIONS AND USAGE

MoviPrep® is an osmotic laxative indicated for cleansing of the colon as a preparation for colonoscopy in adults.

2 DOSAGE AND ADMINISTRATION

2.1 Important Preparation and Administration Instructions

- Correct fluid and electrolyte abnormalities before treatment with MoviPrep [see Warnings and Precautions (5.1)].
- Two doses of MoviPrep are required for a complete preparation for colonoscopy. The time interval between the two doses depends on the regimen prescribed and the planned timing of the colonoscopy procedure. [see Dosage and Administration (2.2, 2.3)].
- The “Split-Dose” is the preferred method and consists of two separate doses: the first dose is taken the evening before the colonoscopy, and the second dose is taken the next day, the morning of the day of the colonoscopy [see Dosage and Administration (2.2)].
- The “Evening Only” is the alternative method and consists of two separate doses: both doses are taken in the evening before the day of the colonoscopy, with a minimum of 1.5 hours between the start of the first dose and the start of the second dose [see Dosage and Administration (2.3)].
- Both MoviPrep dosing regimens require administration of MoviPrep using the mixing container provided to reconstitute the contents of Pouch A and B with water to the Fill Line. Do not reconstitute with other liquids and/or add starch-based thickeners to the mixing container [see Warnings and Precautions (5.7)].
- Additional clear liquids (including water) must be consumed in both dosing regimens [see Dosage and Administration (2.2, 2.3), Warnings and Precautions (5.1)].
- Consume only clear liquids (no solid food) from the start of MoviPrep treatment until after the colonoscopy.
- Do not eat or drink alcohol, milk, anything colored red or purple or any other foods containing pulp material.
- Do not take other laxatives while taking MoviPrep [see Drug Interactions (7.3)].
- Do not take oral medications within 1 hour before or after starting each dose of MoviPrep [see Drug Interactions (7.2)].
- Ensure completion of Dose 2, including all additional liquids, at least 2 hours before the colonoscopy.
- Storage: After reconstitution, store MoviPrep solution in an upright position and keep refrigerated. Use within 24 hours after it is mixed in water.

2.2 Two-Day Split-Dosing Regimen (Preferred Method)

The Two-Day Split-Dosing regimen is the preferred dosing method.

Instruct adult patients that on the day before the clinical procedure, they can consume breakfast, followed by a light lunch (no solid foods), and clear soup and/or plain yogurt for dinner, which must be completed at least 1 hour prior to the start of the first MoviPrep dose.

Instruct adult patients to take two separate doses in conjunction with fluids as follows:

Dose 1 – In the evening before the colonoscopy, approximately 10 to 12 hours before Dose 2:

1. Empty the contents of 1 Pouch A and 1 Pouch B into the mixing container that comes with MoviPrep.
2. Add lukewarm water to the Fill Line on the mixing container (32 fluid ounces). Do not add other ingredients to the MoviPrep solution.
3. Thoroughly mix with a spoon or shake with lid on securely until the contents of Pouch A and B are completely dissolved.
4. Drink 8 ounces of the solution every 15 minutes. This should take about 1 hour. Be sure to drink all the solution.
5. Refill the mixing container halfway to the Fill Line (at least 16 ounces) with a clear liquid and drink all this liquid before going to bed.

Dose 2 – Take next morning, on the day of the colonoscopy, approximately 12 hours after the start of Dose 1 and at least 3 ½ hours prior to colonoscopy:

1. Empty the contents of 1 Pouch A and 1 Pouch B into the mixing container that comes with MoviPrep.
2. Add lukewarm water to the Fill Line on the mixing container (32 fluid ounces). Do not add other ingredients to the MoviPrep solution.
3. Thoroughly mix with a spoon or shake with lid on securely until the contents of Pouch A and B are completely dissolved.
4. Drink 8 ounces of the solution every 15 minutes. This should take about 1 hour. Be sure to drink all of the solution.
5. Refill the mixing container halfway to the Fill Line (at least 16 ounces) with a clear liquid and drink all this liquid at least 2 hours before the colonoscopy.
6. Consume additional water or clear liquids up to 2 hours before the colonoscopy or as prescribed by your healthcare provider. Then stop drinking liquids until after the colonoscopy.
Stop drinking MoviPrep temporarily or drink each portion at longer intervals if severe bloating, abdominal discomfort or distention occurs, until these symptoms resolve.

2.3 One-Day Evening Only Dosing Regimen (Alternative Method)

The One-Day Evening Only regimen is the alternative dosing method for patients for whom the Split-Dosing regimen is inappropriate.

Instruct adult patients that on the day before the clinical procedure, they can consume breakfast, followed by a light lunch (no solid foods), and clear soup and/or plain yogurt for dinner, which must be completed at least 1 hour prior to the start of the first MoviPrep dose.

Instruct adult patients to take two separate doses in conjunction with fluids as follows:

Dose 1 – At least 3 ½ hours before bedtime the evening before the colonoscopy:

1. Empty the contents of 1 Pouch A and 1 Pouch B into the mixing container that comes with MoviPrep.
2. Add lukewarm water to the Fill Line on the mixing container (32 fluid ounces). Do not add other ingredients to the MoviPrep solution.
3. Thoroughly mix with a spoon or shake with lid on securely until the contents of Pouch A and B are completely dissolved.
4. Drink 8 ounces of the solution every 15 minutes. This should take about 1 hour. Be sure to drink all the solution.

Dose 2 – At least 1 ½ hours after starting Dose 1 on the evening before the colonoscopy:

1. Empty the contents of 1 Pouch A and 1 Pouch B into the mixing container that comes with MoviPrep.
2. Add lukewarm water to the Fill Line on the mixing container (32 fluid ounces). Do not add other ingredients to the MoviPrep solution.
3. Thoroughly mix with a spoon or shake with lid on securely until the contents of Pouch A and B are completely dissolved.
4. Drink 8 ounces of the solution every 15 minutes. This should take about 1 hour. Be sure to drink all of the solution.
5. Refill the mixing container to the Fill Line (32 fluid ounces) with a clear liquid and drink all this liquid before going to bed.
6. Consume additional water or clear liquids up to 2 hours before the colonoscopy or as prescribed by your healthcare provider. Then stop drinking liquids until after the colonoscopy.
Stop drinking MoviPrep temporarily or drink each portion at longer intervals if severe bloating, abdominal discomfort or distention occurs, until these symptoms resolve.

3 DOSAGE FORMS AND STRENGTHS

MoviPrep is supplied as a white to yellow powder for reconstitution and is available in a carton that contains 2 pouches labeled Pouch A and 2 pouches labeled Pouch B.

- Each Pouch A contains 100 grams of polyethylene glycol (PEG) 3350, 7.5 grams of sodium sulfate, 2.691 grams of sodium chloride, and 1.015 grams of potassium chloride. Pouch A contains lemon flavoring [see Description (11)].
- Each Pouch B contains 4.7 grams of ascorbic acid and 5.9 grams of sodium ascorbate.

4 CONTRAINDICATIONS

MoviPrep is contraindicated in the following conditions:

- Gastrointestinal (GI) obstruction [see Warnings and Precautions (5.6)]
- Bowel perforation [see Warnings and Precautions (5.6)]
- Gastric retention
- Ileus
- Toxic colitis or toxic megacolon
- Hypersensitivity to any ingredient in MoviPrep [see Warnings and Precautions (5.10) and Description (11)]

5 WARNINGS AND PRECAUTIONS

5.1 Serious Fluid and Electrolyte Abnormalities

Advise patients to hydrate adequately before, during, and after the use of MoviPrep. If a patient develops significant vomiting or signs of dehydration after taking MoviPrep, consider performing post-colonoscopy lab tests (electrolytes, creatinine, and BUN).

Bowel preparations can cause fluid and electrolyte disturbances, which can lead to serious adverse reactions including cardiac arrhythmias, seizures, and renal impairment [see Adverse Reactions (6.2)]. Correct fluid and electrolyte abnormalities before treatment with MoviPrep. MoviPrep should be used with caution in patients using concomitant medications that increase the risk of electrolyte abnormalities [such as diuretics, angiotensin converting enzyme (ACE) inhibitors or angiotensin receptor blockers (ARBs)] or in patients with known or suspected hyponatremia. Consider performing pre-dose and post-colonoscopy laboratory tests (sodium, potassium, calcium, creatinine, and BUN) in these patients [see Drug Interactions (7.1)].

5.2 Cardiac Arrhythmias

There have been rare reports of serious arrhythmias (including atrial fibrillation) associated with the use of ionic osmotic laxative products for bowel preparation. These occur predominantly in patients with underlying cardiac risk factors and electrolyte disturbances. Use caution when prescribing MoviPrep for patients at increased risk of arrhythmias (e.g., patients with a history of prolonged QT, uncontrolled arrhythmias, recent myocardial infarction, unstable angina, congestive heart failure, cardiomyopathy, or electrolyte imbalance). Consider pre-dose and post-colonoscopy ECGs in patients at increased risk of serious cardiac arrhythmias.

5.3 Seizures

There have been rare reports of generalized tonic-clonic seizures and/or loss of consciousness associated with use of bowel preparation products in patients with no prior history of seizures. The seizure cases were associated with electrolyte abnormalities (e.g., hyponatremia, hypokalemia, hypocalcemia, and hypomagnesemia) and low serum osmolality. The neurologic abnormalities resolved with correction of fluid and electrolyte abnormalities.

Use caution when prescribing MoviPrep for patients with a history of seizures and in patients at increased risk of seizure, such as patients taking medications that lower the seizure threshold (e.g., tricyclic antidepressants), patients withdrawing from alcohol or benzodiazepines, or patients with known or suspected hyponatremia [see Drug Interactions (7.1)].

5.4 Use in Patients with Renal Impairment

Use MoviPrep with caution in patients with renal impairment or patients taking concomitant medications that affect renal function (such as diuretics, ACE inhibitors, angiotensin receptor blockers, or nonsteroidal anti-inflammatory drugs) [see Drug Interactions (7.1)]. These patients may be at risk for renal injury. Advise these patients of the importance of adequate hydration before, during, and after use of MoviPrep, and consider performing pre-dose and post-colonoscopy laboratory tests (electrolytes, creatinine, and BUN) in these patients [see Use in Specific Populations (8.6)].

5.5 Colonic Mucosal Ulceration, Ischemic Colitis and Ulcerative Colitis

Osmotic laxatives may produce colonic mucosal aphthous ulcerations, and there have been reports of more serious cases of ischemic colitis requiring hospitalization. Concurrent use of stimulant laxatives and MoviPrep may increase the risk of mucosal ulceration or ischemic colitis and is not recommended. Consider the potential for mucosal ulcerations resulting from the bowel preparation when interpreting colonoscopy findings in patients with known or suspected inflammatory bowel disease.

5.6 Use in Patients with Significant Gastrointestinal Disease

If gastrointestinal obstruction or perforation is suspected, perform appropriate diagnostic studies to rule out these conditions before administering MoviPrep [see Contraindications (4)].

Use with caution in patients with severe ulcerative colitis.

5.7 Aspiration

Patients with impaired gag reflex or other swallowing abnormalities are at risk for regurgitation or aspiration of MoviPrep. Observe these patients during the administration of MoviPrep. Use with caution in these patients.

Do not combine MoviPrep with starch-based thickeners [see Dosage and Administration (2.1)]. Polyethylene glycol (PEG), a component of MoviPrep, when mixed with starch-thickened liquids reduces the viscosity of the starch-thickened liquid. When a PEG-based product used for another indication was mixed in starch-based pre-thickened liquids used in patients with dysphagia, thinning of the liquid occurred and cases of choking and potential aspiration were reported.

5.8 Glucose-6-Phosphate Dehydrogenase (G6PD) Deficiency

Since MoviPrep contains sodium ascorbate and ascorbic acid, MoviPrep should be used with caution in patients with glucose-6-phosphate dehydrogenase (G6PD) deficiency, especially G6PD deficiency patients with an active infection, with a history of hemolysis, or taking concomitant medications known to precipitate hemolytic reactions.

5.9 Risks in Patients with Phenylketonuria

Phenylalanine can be harmful to patients with phenylketonuria (PKU). MoviPrep contains phenylalanine, a component of aspartame. Each MoviPrep treatment contains 131 mg of phenylalanine (after hydrolysis of the aspartame molecule in vivo to aspartic acid and phenylalanine). Before prescribing MoviPrep to a patient with PKU, consider the combined daily amount of phenylalanine from all sources, including MoviPrep.

5.10 Hypersensitivity Reactions

MoviPrep contains polyethylene glycol (PEG) and lemon flavoring (containing citral, lime oil, maltodextrin, acacia gum, vitamin E, and other natural flavoring agents) and may cause serious hypersensitivity reactions including anaphylaxis, angioedema, rash, urticaria, and pruritus [see Contraindications (4), Adverse Reactions (6.2) and Description (11)]. Inform patients of the signs and symptoms of anaphylaxis and instruct them to seek immediate medical care should signs and symptoms occur.

6 ADVERSE REACTIONS

The following serious or otherwise important adverse reactions for bowel preparations are described elsewhere in the labeling:

- Serious Fluid and Electrolyte Abnormalities [see Warnings and Precautions (5.1)]
- Cardiac Arrhythmias [see Warnings and Precautions (5.2)]
- Seizures [see Warnings and Precautions (5.3)]
- Patients with Renal Impairment [see Warnings and Precautions (5.4)]
- Colonic Mucosal Ulceration, Ischemic Colitis and Ulcerative Colitis [see Warnings and Precautions (5.5)]
- Patients with Significant Gastrointestinal Disease [see Warnings and Precautions (5.6)]
- Aspiration [see Warnings and Precautions (5.7)]
- Glucose-6-Phosphate Dehydrogenase (G6PD) Deficiency [see Warnings and Precautions (5.8)]
- Risks in Patients with Phenylketonuria [see Warnings and Precautions (5.9)]
- Hypersensitivity Reactions [see Warnings and Precautions (5.10)]

6.1 Clinical Studies Experience

Because clinical trials are conducted under widely varying conditions, adverse reaction rates observed in the clinical trials of a drug cannot be directly compared to rates in the clinical trials of another drug and may not reflect the rates observed in clinical practice.

The safety of MoviPrep as a Two-Day Split-Dosing and One-Day Evening Only Dosing Regimen was evaluated in two randomized, active-controlled, multicenter, investigator-blinded clinical trials in adult patients scheduled to have an elective colonoscopy [see Clinical Studies (14)]. The safety analysis for Study 1 included 359 adult patients ranging in age from 18 to 88 years (mean age 59), with 52% female and 48% male patients. The safety analysis for Study 2 included 340 adult patients ranging in age from 21 to 76 years (mean age 53), with 53% male and 47% female patients.

Tables 1 and 2 display adverse reactions reported in at least 2% and 5% of patients in either treatment group in Study 1 and Study 2, respectively. Since diarrhea was considered as a part of the efficacy assessment, it was not defined as an adverse reaction in these trials.

Table 1: Common Adverse Reactions [Reported in at least 2% of patients in either treatment group] in Patients Undergoing Colonoscopy in Study 1
 | MoviPrep Two-Day Split Dosing Regimen (N=180) | 4 Liter PEG + Electrolytes Solution (N=179)
Malaise | 19% | 18%
Nausea | 14% | 20%
Abdominal pain | 13% | 15%
Vomiting | 8% | 13%
Upper abdominal pain | 6% | 6%
Dyspepsia | 3% | 1%

Table 2: Common Adverse Reactions [Reported in at least 5% of patients in either treatment group] [Patients were specifically asked about the occurrence of the following symptoms: shivering, anal irritations, abdominal bloating or fullness, sleep loss, nausea, vomiting, weakness, hunger sensation, abdominal cramps or pain, thirst sensation, and dizziness.] in Patients Undergoing Colonoscopy in Study 2
 | MoviPrep One-Day Evening Only; Dosing Regimen (N=169) | 90 mL Oral Sodium Phosphate Solution (N=171)
Abdominal distension | 60% | 41%
Anal discomfort | 51% | 52%
Thirst | 47% | 65%
Nausea | 47% | 47%
Abdominal pain | 39% | 32%
Sleep disorder | 35% | 29%
Rigors | 34% | 30%
Hunger | 30% | 71%
Malaise | 27% | 53%
Vomiting | 7% | 8%
Dizziness | 7% | 18%
Headache | 2% | 5%
Hypokalemia | 0% | 6%
Hyperphosphatemia | 0% | 6%

6.2 Postmarketing Experience

The following adverse reactions have been identified during post-approval use of MoviPrep or other PEG-based products. Because these reactions are reported voluntarily from a population of uncertain size, it is not always possible to reliably estimate their frequency or establish a causal relationship to drug exposure.

Cardiovascular: tachycardia, palpitations, hypertension, arrhythmia, atrial fibrillation, peripheral edema, asystole, acute pulmonary edema and syncope, and dehydration.

Gastrointestinal: upper gastrointestinal bleeding from a Mallory-Weiss tear, esophageal perforation [usually with gastroesophageal reflux disease (GERD)].

Hypersensitivity reactions: anaphylaxis (some of which were severe, including shock), rash, urticaria, pruritus, lip, tongue and facial swelling, dyspnea, chest tightness and throat tightness, rhinorrhea, dermatitis, fever, and chills [see Warnings and Precautions (5.10)].

Nervous system: tremor, seizure.

Renal: renal impairment and/or failure.

7 DRUG INTERACTIONS

7.1 Drugs That May Increase Risks due to Fluid and Electrolyte Abnormalities

Use caution when prescribing MoviPrep for patients with conditions and/or who are using medications that increase the risk for fluid and electrolyte disturbances or may increase the risk of renal impairment, seizures, arrhythmias, or QT prolongation in the setting of fluid and electrolyte abnormalities [see Warnings and Precautions (5.1, 5.2, 5.3, 5.4)]. Consider additional patient evaluations as appropriate.

7.2 Potential for Reduced Drug Absorption

MoviPrep can reduce the absorption of other co-administered drugs. Administer oral medications at least 1 hour before the start of administration of each dose of MoviPrep [see Dosage and Administration (2.1)].

7.3 Stimulant Laxatives

Concurrent use of stimulant laxatives and MoviPrep may increase the risk of mucosal ulceration or ischemic colitis. Avoid use of stimulant laxatives (e.g., bisacodyl, sodium picosulfate) while taking MoviPrep [see Warnings and Precautions (5.5, 5.6)].

8 USE IN SPECIFIC POPULATIONS

8.1 Pregnancy

Risk Summary

There are no available data on MoviPrep in pregnant women to inform a drug-associated risk for adverse developmental outcomes. Animal reproduction studies have not been conducted with MoviPrep.

The estimated background risk of major birth defects and miscarriage for the indicated population is unknown. All pregnancies have a background risk of birth defect, loss, or other adverse outcomes. In the U.S. general population, the estimated background risk of major birth defects and miscarriage in clinically recognized pregnancies is 2% to 4% and 15% to 20%, respectively.

8.2 Lactation

Risk Summary

There are no data available on the presence of MoviPrep in human milk, the effects of the drug on the breastfed child, or the effects of the drug on milk production. The lack of clinical data during lactation precludes a clear determination of the risk of MoviPrep to a child during lactation; therefore, the developmental and health benefits of breastfeeding should be considered along with the mother’s clinical need for MoviPrep and any potential adverse effects on the breastfed child from MoviPrep or from the underlying maternal condition.

8.4 Pediatric Use

The safety and effectiveness of MoviPrep in pediatric patients have not been established.

8.5 Geriatric Use

Of the 413 patients in clinical trials receiving MoviPrep, 91 (22%) patients were aged 65 or older, while 25 (6%) patients were over 75 years of age. No overall differences in safety or effectiveness were observed between geriatric patients and younger patients, and other reported clinical experience has not identified differences in responses between geriatric patients and younger patients. However, elderly patients are more likely to have decreased hepatic, renal or cardiac function and may be more susceptible to adverse reactions resulting from fluid and electrolyte abnormalities [see Warnings and Precautions (5.1)].

8.6 Renal Impairment

Use MoviPrep with caution in patients with renal impairment or patients taking concomitant medications that may affect renal function [see Drug Interactions (7.1)]. These patients may be at risk for renal injury. Advise these patients of the importance of adequate hydration before, during and after the use of MoviPrep, and consider performing baseline and post-colonoscopy laboratory tests (electrolytes, creatinine, and BUN) in these patients [see Warnings and Precautions (5.4)].

10 OVERDOSAGE

Overdosage of more than the recommended dose of MoviPrep may lead to severe electrolyte disturbances, including hyponatremia and/or hypokalemia, as well as dehydration and hypovolemia, with signs and symptoms of these disturbances. Certain severe electrolyte disturbances may lead to cardiac arrhythmias, seizures, and renal failure [see Warnings and Precautions (5.1, 5.2, 5.3)]. Monitor for fluid and electrolyte disturbances and treat symptomatically.

11 DESCRIPTION

MoviPrep (polyethylene glycol 3350, sodium sulfate, sodium chloride, potassium chloride, sodium ascorbate, and ascorbic acid for oral solution) is an osmotic laxative consisting of 4 pouches (2 of Pouch A and 2 of Pouch B) containing white to yellow powder for reconstitution.

Each Pouch A contains 100 grams of polyethylene glycol (PEG) 3350, 7.5 grams of sodium sulfate, 2.691 grams of sodium chloride, and 1.015 grams of potassium chloride, plus the following excipients: aspartame (sweetener), acesulfame potassium (sweetener), and lemon flavoring containing citral, lime oil, maltodextrin, acacia gum, vitamin E, and other natural flavoring agents. Pouch A contains 111.9 g of powder for oral solution.

Each Pouch B contains 4.7 grams of ascorbic acid and 5.9 grams of sodium ascorbate. Pouch B contains 10.6 g of powder for oral solution.

When 1 Pouch A and 1 Pouch B are dissolved together in water to a volume of 1 liter, MoviPrep (polyethylene glycol 3350, sodium sulfate, sodium chloride, potassium chloride, sodium ascorbate, and ascorbic acid) is an oral solution having a lemon taste.

The entire, reconstituted, 2-liter MoviPrep colon preparation contains 200 grams of polyethylene glycol (PEG) 3350, 15 grams of sodium sulfate, 5.38 grams of sodium chloride, 2.03 grams of potassium chloride, 9.4 grams of ascorbic acid, and 11.8 grams of sodium ascorbate plus the following excipients: aspartame (sweetener), acesulfame potassium (sweetener), and lemon flavoring.

A mixing container for reconstitution is enclosed.

Phenylketonurics: Contains Phenylalanine 131 mg per treatment.

12 CLINICAL PHARMACOLOGY

12.1 Mechanism of Action

The primary mode of action is osmotic action of polyethylene glycol 3350, sodium sulfate, sodium chloride, potassium chloride, sodium ascorbate, and ascorbic acid, which induce a laxative effect. The physiological consequence is increased water retention in the lumen of the colon, resulting in loose stools.

14 CLINICAL STUDIES

The colon cleansing efficacy and safety of MoviPrep was evaluated in two randomized, actively-controlled, multi-center, investigator-blinded trials in adult patients scheduled to have an elective colonoscopy.

In Study 1, patients were randomized to one of the following two colon preparation treatments: 1) 2 liters of MoviPrep with 1 additional liter of clear liquid split into two doses (during the evening before and the morning of the colonoscopy) and 2) 4 liters of polyethylene glycol plus electrolytes solution (4L PEG + E) split into two doses (during the evening before and the morning of the colonoscopy). Patients were allowed to have a morning breakfast, a light lunch, clear soup and/or plain yogurt for dinner. Dinner had to be completed at least one hour prior to initiation of the colon preparation administration.

The primary efficacy endpoint was the proportion of patients with effective colon cleansing as judged by blinded gastroenterologists on the basis of videotapes recorded during the colonoscopy.

The blinded gastroenterologists graded the colon cleansing twice (during introduction and withdrawal of the colonoscope) and the poorer of the two assessments was used in the primary efficacy analysis.

The efficacy analysis included 308 adult patients who had an elective colonoscopy. Patients ranged in age from 18 to 88 years old (mean age about 59 years old) with 52% female and 48% male patients. Table 3 displays the results.

Table 3: Effectiveness of Overall Colon Cleansing of MoviPrep vs. 4 Liter Polyethylene Glycol plus Electrolytes Solution in Study 1
 | Responders A^2 or B^3 (%) | C^4 (%) | D^5 (%)
MoviPrep (N=153) | 88.9 | 9.8 | 1.3
4L PEG + E^1 (N=155) | 94.8 | 4.5 | 0.6

1 4L PEG + E is 4 Liter Polyethylene Glycol plus Electrolytes Solution.
2 A: colon empty and clean or presence of clear liquid, but easily removed by suction
3 B: brown liquid or semisolid remaining amounts of stool, fully removable by suction or displaceable, thus allowing a complete visualization of the gut mucosa
4 C: semisolid amounts of stool, only partially removable with a risk of incomplete visualization of the gut mucosa
5 D: semisolid or solid amounts of stool; consequently colonoscopy incomplete or needed to be terminated.

4L PEG+E’s responder rate was not significantly higher than MoviPrep’s responder rate.

In Study 2, patients were randomized to one of the following two colon preparation treatments: 1) 2 liters of MoviPrep with 1 additional liter of clear liquid in the evening prior to the colonoscopy and 2) 90 mL of oral sodium phosphate solution (90 mL OSPS) with at least 2 liters of additional clear liquid during the day and evening prior to the colonoscopy. Patients randomized to MoviPrep therapy were allowed to have a morning breakfast; a light lunch; and clear soup and/or plain yogurt for dinner. Dinner had to be completed at least one hour prior to initiation of the colon preparation administration.

The primary efficacy endpoint was the proportion of patients with effective colon cleansing as judged by the colonoscopist and one blinded gastroenterologist (on the basis of videotapes recorded during the colonoscopy). In case of a discrepancy between the colonoscopist and the blinded gastroenterologist, a second blinded gastroenterologist made the final efficacy determination.

The efficacy analysis included 280 adult patients who had an elective colonoscopy. Patients ranged in age from 21 to 76 years old (mean age about 53 years old) with 47% female and 53% male patients. Table 4 displays the results.

Table 4: Effectiveness of Overall Colon Cleansing of MoviPrep vs. 90 mL Oral Sodium Phosphate Solution in Study 2
 | Responders A^2 or B^3 (%) | C^4 (%) | D^5 (%)
MoviPrep (N=137) | 73.0 | 23.4 | 3.6
90 mL OSPS^1 (N=143) | 64.4 | 29.4 | 6.3

1 OSPS is Oral Sodium Phosphate Solution.
2 A: empty and clean or clear liquid (transparent, yellow, or green)
3 B: brown liquid or semisolid remaining small amounts of stool, fully removable by suction or displaceable allowing a complete visualization of the underlying mucosa
4 C: semisolid only partially removable/displaceable stools; risk of incomplete examination of the underlying mucosa
5 D: heavy and hard stool making the segment examination uninterpretable and, consequently, the colonoscopy needed to be terminated.

MoviPrep’s responder rate was not significantly higher than OSPS’s responder rate.

16 HOW SUPPLIED/STORAGE AND HANDLING

MoviPrep (polyethylene glycol 3350, sodium sulfate, sodium chloride, potassium chloride, sodium ascorbate, and ascorbic acid for oral solution) is supplied as a white to yellow powder for reconstitution and is lemon flavored.

NDC 65649-201-75, MoviPrep, single-use outer carton:

- Each outer carton contains a disposable mixing container with lid for reconstitution of MoviPrep, prescribing information and patient information, and one inner carton.
- Each inner carton contains 2 pouches labeled Pouch A and 2 pouches labeled Pouch B.

Storage

Store carton/container at room temperature, between 20° to 25°C (68° to 77°F); excursions permitted to 15° to 30°C (59° to 86°F). When reconstituted, store upright and keep solution refrigerated. Use within 24 hours [see Dosage and Administration (2.1)].

17 PATIENT COUNSELING INFORMATION

Advise the patient to read the FDA-approved patient labeling (Medication Guide and Instructions for Use).

Instruct patients:

- That two doses of MoviPrep are required for a complete preparation for colonoscopy either as a Split-Dose (2-Day), or Evening Only (1-Day) dosing regimen [see Instructions for Use].
- Not to take other laxatives while they are taking MoviPrep.
- That MoviPrep contains 131 mg of phenylalanine per treatment [see Warnings and Precautions (5.9)].
- That each pouch needs to be reconstituted in water before ingestion and that they should drink additional clear liquids. Examples of clear liquids can be found in the Instructions for Use.
- Not to take oral medications within one hour of starting each dose of MoviPrep.
- To follow the directions in the Instructions for Use, for either the Two-Day Split-Dosing or the One-Day Evening Only Dosing regimen, as prescribed.
- To consume additional clear liquids before, during, and after the use of MoviPrep to prevent dehydration [see Warnings and Precautions (5.1)].
- To contact their healthcare provider if they develop significant vomiting or signs of dehydration after taking MoviPrep or if they experience altered consciousness or seizures [see Warnings and Precautions (5.1, 5.2, 5.3, 5.4)]
- Not to eat or drink alcohol, milk, anything colored red or purple or any other foods containing pulp material.
- To stop drinking MoviPrep temporarily or drink each portion at longer intervals if they develop severe abdominal discomfort or distention until these symptoms diminish. If severe symptoms persist, tell patients to contact their healthcare provider.

Distributed by:

Salix Pharmaceuticals, a division of
Bausch Health US, LLC
Bridgewater, NJ 08807 USA

MoviPrep is a registered trademark of Velinor AG used under license.

© 2025 Salix Pharmaceuticals, Inc. or its affiliates

9656606 70015787-02

MEDICATION GUIDE

MoviPrep® (moo-vee-prěp)
(polyethylene glycol 3350, sodium sulfate, sodium chloride, potassium chloride, sodium ascorbate, and ascorbic acid for oral solution)

Read this Medication Guide and Instructions for Use before your colonoscopy and again before you start taking MoviPrep.

What is the most important information I should know about MoviPrep?

MoviPrep and other bowel preparations can cause serious side effects, including:

- Serious loss of body fluid (dehydration) and changes in blood salts (electrolytes) in your blood. These changes can cause:
- abnormal heartbeats that can cause death.
- seizures. This can happen even if you have never had a seizure.
- kidney problems.

Your chance of having fluid loss and changes in body salts with MoviPrep is higher if you:

- have heart problems.
- have kidney problems.
- take water pills (diuretics), high blood pressure medicine, or non-steroidal anti-inflammatory drugs (NSAIDs).

Tell your healthcare provider right away if you have any of these symptoms of serious loss of body fluid (dehydration) while taking MoviPrep:

- vomiting
- urinating less often than normal
- dizziness
- headache
See “What are the possible side effects of MoviPrep?” for more information about side effects.

What is MoviPrep?

MoviPrep is a prescription medicine used by adults to clean the colon before a colonoscopy. MoviPrep cleans your colon by causing you to have diarrhea (loose stools). Cleaning your colon helps your healthcare provider see the inside of your colon more clearly during your colonoscopy.

It is not known if MoviPrep is safe and effective in children.

Who should not take MoviPrep?

Do not take MoviPrep if your healthcare provider has told you that you have:

- a blockage in your intestine (bowel obstruction).
- an opening in the wall of your stomach or intestine (bowel perforation).
- problems with food and fluid emptying from your stomach (gastric retention).
- a problem with food moving too slowly through your intestines (ileus).
- a very dilated intestine (toxic megacolon).
- an allergy to any of the ingredients in MoviPrep. See the end of this Medication Guide for a complete list of ingredients in MoviPrep.

What should I tell my healthcare provider before taking MoviPrep?

Before taking MoviPrep, tell your healthcare provider about all of your medical conditions, including if you:

- have problems with serious loss of body fluid (dehydration) and changes in blood salts (electrolytes).
- have heart problems.
- have seizures or take medicines for seizures.
- have kidney problems or take medicines for kidney problems.
- have stomach or bowel problems, including ulcerative colitis.
- have problems with swallowing, gastric reflux, or if you inhale food or fluid into your lungs when eating or drinking (aspirate).
- have a condition called glucose-6-phosphate dehydrogenase (G6PD) deficiency that destroys red blood cells.
- are withdrawing from alcohol or benzodiazepines.
- have phenylketonuria (PKU). MoviPrep contains phenylalanine.
- are allergic to any of the ingredients in MoviPrep.
- are pregnant or plan to become pregnant. It is not known if MoviPrep will harm your unborn baby. Talk to your healthcare provider if you are pregnant.
- are breastfeeding or plan to breastfeed. It is not known if MoviPrep passes into your breast milk. You and your healthcare provider should decide if you will take MoviPrep while breastfeeding.

Tell your healthcare provider about all the medicines you take, including prescription and over-the-counter medicines, vitamins, and herbal supplements.

MoviPrep may affect how other medicines work. Do not take medicines by mouth 1 hour before or after starting each dose of MoviPrep.

Especially tell your healthcare provider if you take:

- medicines to treat a blood salt (electrolyte) imbalance.
- medicines for blood pressure or heart problems.
- medicines for seizures (antiepileptics).
- medicines for kidney problems.
- water pills (diuretics).
- non-steroidal anti-inflammatory drugs (NSAIDs).
- laxatives. Do not take other laxatives while taking MoviPrep.
- medicines for depression or other mental health problems.
- starch-based thickeners. For people who have trouble swallowing, do not mix MoviPrep with starch-based thickeners.

Ask your healthcare provider or pharmacist for a list of these medicines if you are not sure if you are taking any of the medicines listed above.

Know the medicines you take. Keep a list of them to show your healthcare provider and pharmacist when you get a new medicine.

How should I take MoviPrep?

See the Instructions for Use for dosing instructions. You must read, understand, and follow these instructions to take MoviPrep the right way.

- Take MoviPrep exactly as your healthcare provider tells you to take it. Your healthcare provider will tell you to take the Two-Day Split-Dosing regimen option or the One-Day Evening Only Dosing regimen option.
- On the day before the procedure, you can have breakfast, followed by a light lunch (no solid foods), and dinner of clear soup with or without plain yogurt, or plain yogurt only. You must finish dinner at least 1 hour before the start of the first MoviPrep dose.
- Drink only clear liquids before, during, and after you take MoviPrep, until 2 hours before your colonoscopy to help prevent fluid loss (dehydration).
- Do not eat solid food while taking MoviPrep until after your colonoscopy.
- Do not eat or drink alcohol, milk, anything colored red or purple or any other foods with pulp.
- It is important for you to drink the additional amount of clear liquids listed in the Instructions for Use.
- You may have stomach-area (abdomen) bloating after your first dose of MoviPrep.
  - If you have severe stomach-area (abdomen) discomfort or bloating, stop drinking MoviPrep for a short time or wait a longer time between each dose of MoviPrep until your stomach-area symptoms improve. If your stomach-area discomfort or bloating continues, tell your healthcare provider.
- If you take too much MoviPrep, call your healthcare provider.

What are the possible side effects of MoviPrep?

MoviPrep can cause serious side effects, including:

- Changes in certain blood tests. Your healthcare provider may do blood tests after you take MoviPrep to check your blood for changes. Tell your healthcare provider if you have any symptoms of too much fluid loss, including:

- vomiting
- seizures
- kidney problems

- heart problems
- dizziness
- dry mouth

- feel faint, weak or lightheaded especially when you stand up (orthostatic hypotension)

- Ulcers of the bowel or bowel problems (ischemic colitis). Tell your healthcare provider right away if you have severe stomach-area (abdomen) pain or rectal bleeding.
- Serious allergic reactions. Symptoms of a serious allergic reaction may include:

- skin rash
- raised red patches on your skin (hives)
- kidney problems
- swelling of the face, lips, tongue and throat
- itching

The most common side effects of MoviPrep include:

- anal discomfort
- vomiting
- chills
- nausea
- dizziness
- stomach-area (abdomen pain or bloating)
- discomfort

- sleep problems
- thirst
- indigestion
- hunger

These are not all the possible side effects of MoviPrep.

Call your doctor for medical advice about side effects. You may report side effects to FDA at 1-800-FDA-1088.

How should I store MoviPrep?

- Store MoviPrep that has not been mixed with water at room temperature, between 68°F to 77°F (20°C to 25°C).
- Store MoviPrep that has been mixed with water in an upright position in the refrigerator.
- MoviPrep should be taken within 24 hours after it has been mixed with water.

Keep MoviPrep and all medicines out of the reach of children.

General information about the safe and effective use of MoviPrep.

Medicines are sometimes prescribed for purposes other than those listed in a Medication Guide. Do not use MoviPrep for a condition for which it was not prescribed. Do not give MoviPrep to other people, even if they are going to have the same procedure you are. It may harm them.

This Medication Guide summarizes the most important information about MoviPrep. If you would like more information, talk with your healthcare provider. You can ask your pharmacist or healthcare provider for information that is written for health professionals.

For more information, call 1-800-321-4576 or go to www.MoviPrep.com.

What are the ingredients in MoviPrep?

Active ingredients:

Pouch A: polyethylene glycol (PEG) 3350, sodium sulfate, sodium chloride, potassium chloride.

Pouch B: ascorbic acid and sodium ascorbate.

Inactive ingredients:

Pouch A: aspartame, acesulfame potassium, and lemon flavoring including citral, lime oil, maltodextrin, acacia gum, vitamin E, and other natural flavoring agents.

Distributed by:
Salix Pharmaceuticals, a division of
Bausch Health US, LLC
Bridgewater, NJ 08807 USA

MoviPrep is a registered trademark of Velinor AG used under license.

© 2025 Salix Pharmaceuticals, Inc. or its affiliates

This Medication Guide has been approved by the U.S. Food and Drug Administration.
Revised: October 2025
9656606 70015787-02

INSTRUCTIONS FOR USE

MoviPrep® (polyethylene glycol 3350, sodium sulfate, sodium chloride, potassium chloride, sodium ascorbate, and ascorbic acid for oral solution)

There are two different options for taking MoviPrep. Your healthcare provider will tell you to take the Two-Day Split-Dosing Regimen option or the One-Day Evening Only Dosing Regimen option.

Important Information on MoviPrep:
2. water
3. clear fruit juices without pulp including apple, white grape, or white cranberry
4. strained limeade or lemonade
5. coffee or tea (do not use any dairy or non-dairy creamer)
6. clear broth
7. clear soda
8. gelatin (without added fruit or topping, no red or purple)
9. popsicles (without pieces of fruit or pulp, no red or purple)
10. You must drink all of the Dose 1 and Dose 2 of MoviPrep with either dosing regimen option. Make sure you finish Dose 2 at least 2 hours before your colonoscopy.
11. After completing Dose 2, it is important that you drink additional clear liquids (including water), but you must stop drinking all liquids at least 2 hours before your colonoscopy.
12. MoviPrep is lemon flavored containing citral, lime oil, maltodextrin, acacia gum, vitamin E, and other natural flavoring agents.
13. MoviPrep must be mixed with water. Do not add any other ingredients to MoviPrep.
14. Do not mix MoviPrep with starch-based thickeners.
15. After you start taking MoviPrep, you can only drink clear liquids (no solid foods) until after your colonoscopy. Examples of clear liquids include:
16. water
17. clear fruit juices without pulp including apple, white grape, or white cranberry
18. strained limeade or lemonade
19. coffee or tea (do not use any dairy or non-dairy creamer)
20. clear broth
21. clear soda
22. gelatin (without added fruit or topping, no red or purple)
23. popsicles (without pieces of fruit or pulp, no red or purple)
24. Drink plenty of clear liquids before, during, and after you take MoviPrep, up until 2 hours before your colonoscopy, to help prevent fluid loss (dehydration).
25. Do not eat or drink anything within 2 hours before your colonoscopy.
26. Do not eat or drink alcohol, milk, anything colored red or purple or containing pulp.
27. Do not take other laxatives while taking MoviPrep.
28. Do not take any medicines by mouth (oral) within 1 hour before or after starting each dose of MoviPrep.
29. Do not eat any solid food while taking MoviPrep until after your colonoscopy.

To take each dose of MoviPrep, you will need:

- Mixing Container that comes with MoviPrep
- One Pouch A
- One Pouch B
- Lukewarm water
- For the Two-Day Split-Dosing Regimen:
  - On the day before the colonoscopy you can eat breakfast followed by a light lunch (no solid foods). For dinner you may have a clear soup with or without plain yogurt, or plain yogurt only.
  - You must finish eating at least 1 hour before you start taking MoviPrep.
  - You must take the first dose between 10 to 12 hours before the second dose. The second dose must be taken at least 3 ½ hours before the colonoscopy.
  - After you start taking MoviPrep you can only drink clear liquids.
- For the One-Day Evening Only Dosing Regimen:
  - On the day before the colonoscopy you can eat breakfast followed by a light lunch. For dinner you may have a clear soup with or without plain yogurt, or plain yogurt only.
  - You must finish eating at least 1 hour before you start taking MoviPrep.
  - You must take the first dose 3 ½ hours before bedtime the evening before the colonoscopy.
  - After you start taking MoviPrep you can only drink clear liquids.
  - Take the second dose 1 ½ hours after starting Dose 1.

Two-Day Split-Dosing Regimen Dosing Instructions

Dose 1 – Take this dose the evening before your colonoscopy (10 to 12 hours before Dose 2):

Step 1: Empty the contents of one Pouch A and one Pouch B into the Mixing Container that comes with MoviPrep.

Step 2: Add lukewarm water to the Fill Line on the Mixing Container. You will need at least 32 ounces.

Step 3: Mix to completely dissolve the medicine from Pouch A and Pouch B into the lukewarm water. To mix the solution, stir the medicine in the Mixing Container with a spoon, or close the lid and shake.

Step 4: Drink one 8 oz. (ounce) glass of the solution every 15 minutes. Be sure to drink all of the solution in the Mixing Container. It should take about 1 hour to drink all the liquid.

If you feel like you have severe stomach pain or discomfort you can stop taking MoviPrep for a short period of time and then continue taking it or you can take smaller sips of MoviPrep so that you space out your dose longer than 1 hour. If you still have severe stomach pain, call your healthcare provider.

Step 5: Refill the Mixing Container with 16 oz. (at least halfway to Fill Line and enough for two 8 oz. glasses) of a clear liquid and drink all of this liquid before you go to bed.

Dose 2 – Take this dose the next morning on the day of your colonoscopy (start at least 3 ½ hours before your colonoscopy):
Step 1: Repeat steps 1 through 4 from Dose 1 of the Split-Dose (2-Day) instructions.
Step 2: Fill the Mixing Container with 16 oz. (at least halfway to Fill Line and enough for two 8 oz. glasses) of a clear liquid and drink all of this liquid at least 2 hours before your colonoscopy.

Step 3: Drink only clear liquids up to 2 hours before your colonoscopy or as prescribed by your healthcare provider. Then stop drinking liquids until after your colonoscopy.

One-Day Evening Only Dosing Regimen Instructions

Dose 1 (take at least 3 ½ hours before bedtime the evening before your colonoscopy):

Step 1: Empty the contents of one Pouch A and one Pouch B into the Mixing Container that comes with MoviPrep.

Step 2: Add lukewarm water to the Fill Line on the Mixing Container. You will need at least 32 ounces.

Step 3: Mix to completely dissolve the medicine from Pouch A and Pouch B into the lukewarm water. To mix the solution, stir the medicine in the Mixing Container with a spoon, or close the lid and shake.

Step 4: Drink one 8 oz. (ounce) glass of the solution every 15 minutes. Be sure to drink all of the solution in the Mixing Container. It should take about 1 hour to drink all the liquid.

If you feel like you have severe stomach pain or discomfort you can stop taking MoviPrep for a short period of time and then continue taking it or you can take smaller sips of MoviPrep so that you space out your dose longer than 1 hour. If you still have severe stomach pain, call your healthcare provider.

Dose 2 (take about 1 ½ hours after starting Dose 1):

Step 1: Repeat Steps 1 through 4 from Dose 1 of the Evening Only (1-Day) instructions.
Step 2: After you complete steps 1 through 4, fill the Mixing Container again to the Fill Line with clear liquid and drink all of this liquid before you go to bed.

Step 3: Drink only clear liquids up to 2 hours before your colonoscopy or as prescribed by your healthcare provider. Then stop drinking liquids until after your colonoscopy.

Distributed by:
Salix Pharmaceuticals, a division of
Bausch Health US, LLC
Bridgewater, NJ 08807 USA

MoviPrep is a registered trademark of Velinor AG used under license.

© 2025 Salix Pharmaceuticals, Inc. or its affiliates

This Instructions for Use has been approved by the U.S. Food and Drug Administration.

Revised: October 2025
  9656606 70015787-02

PACKAGE LABEL PRINCIPAL DISPLAY PANEL - MoviPrep Outer Carton

Rx only

NDC 65649-201-75

MoviPrep®
(PEG-3350, Sodium Sulfate, Sodium Chloride, Potassium Chloride,
Sodium Ascorbate and Ascorbic Acid for Oral Solution)
100 g/7.5 g/2.691 g/1.015 g/5.9 g/4.7 g

Phenylketonurics:
contains phenylalanine – a maximum of 131 mg per course of treatment.

PHARMACIST: Dispense the enclosed
Medication Guide to each patient.

Keep out of reach of children.

This carton contains: One container to mix MoviPrep®

2 Pouches Labeled
Pouch A:
PEG-3350 100 g
Sodium sulfate 7.5g
Sodium chloride 2.691 g
Potassium chloride 1.015 g
also contains aspartame
2 Pouches Labeled
Pouch B:
Sodium ascorbate 5.9 g
Ascorbic acid 4.7 g
On mixing in 1 liter of water, one
Pouch A and one Pouch B provide:
PEG-3350 29.6 mmol/L
Sodium 181.6 mmol/L
Chloride 59.8 mmol/L
Sulfate 52.8 mmol/L
Potassium 14.2 mmol/L
Ascorbate 29.8 mmol/L

9656205
70016298-02